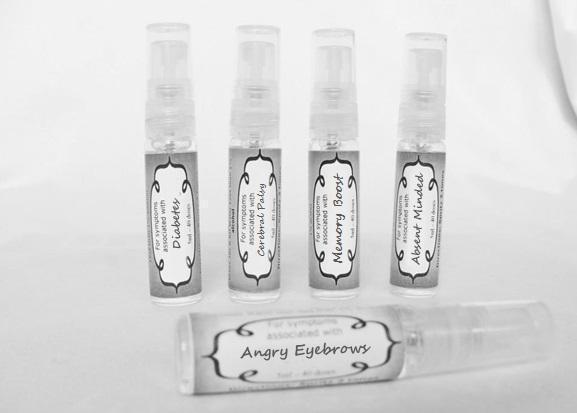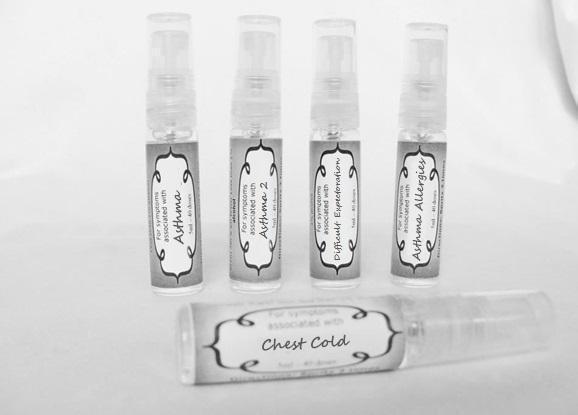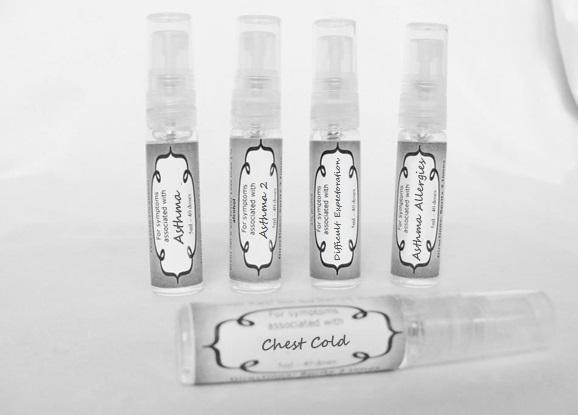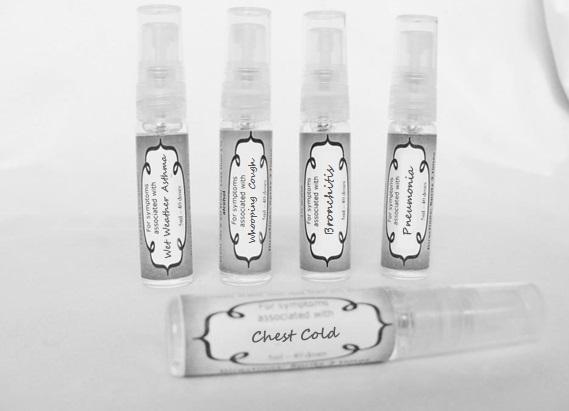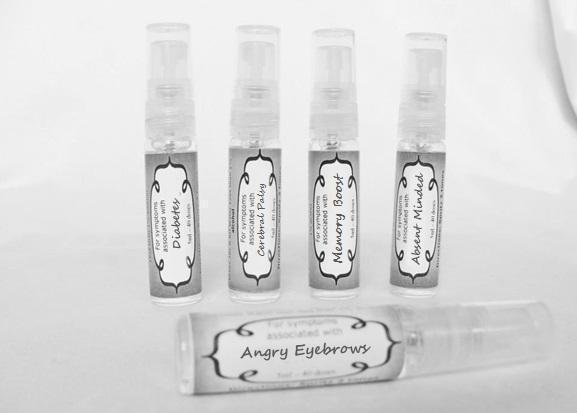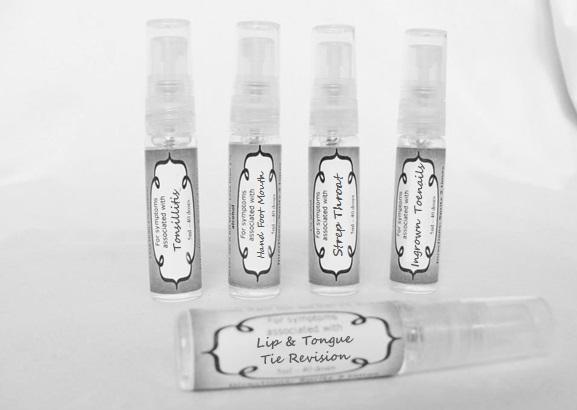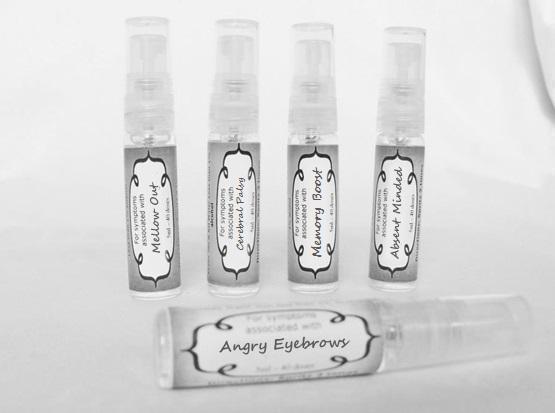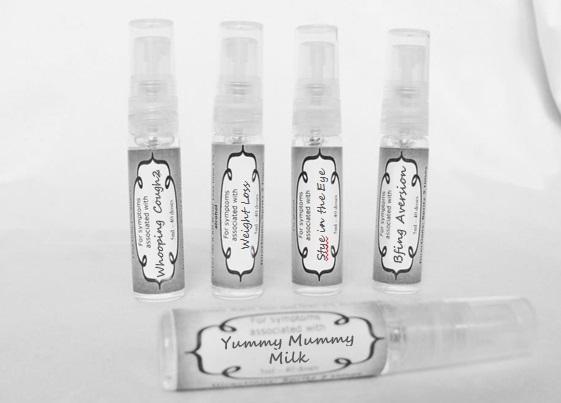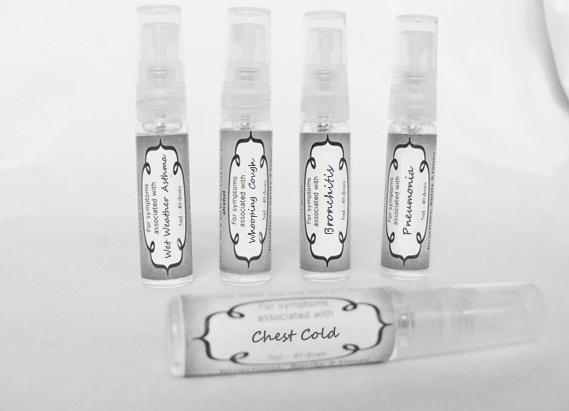 DRUG LABEL: Asthma
NDC: 59667-0089 | Form: SPRAY
Manufacturer: Home Sweet Homeopathics
Category: homeopathic | Type: HUMAN OTC DRUG LABEL
Date: 20130802

ACTIVE INGREDIENTS: TSUGA CANADENSIS BARK 30 [hp_C]/30 [hp_C]; EPINEPHRINE 30 [hp_C]/30 [hp_C]; AMMI VISNAGA FRUIT 30 [hp_C]/30 [hp_C]; FELIS CATUS HAIR 30 [hp_C]/30 [hp_C]; ERIODICTYON CALIFORNICUM LEAF 30 [hp_C]/30 [hp_C]; EUCALYPTUS GLOBULUS LEAF 30 [hp_C]/30 [hp_C]; HUMAN DANDER 30 [hp_C]/30 [hp_C]; DERMATOPHAGOIDES FARINAE 30 [hp_C]/30 [hp_C]; DERMATOPHAGOIDES PTERONYSSINUS 30 [hp_C]/30 [hp_C]; OKOUBAKA AUBREVILLEI BARK 30 [hp_C]/30 [hp_C]; ORIGANUM MAJORANA WHOLE 30 [hp_C]/30 [hp_C]; MELISSA OFFICINALIS 30 [hp_C]/30 [hp_C]; MYRTUS COMMUNIS TOP 30 [hp_C]/30 [hp_C]; MENTHA PIPERITA 30 [hp_C]/30 [hp_C]; PINUS SYLVESTRIS LEAFY TWIG 30 [hp_C]/30 [hp_C]
INACTIVE INGREDIENTS: WATER; ALCOHOL

PURPOSE

For symptoms associated with

To be used according to label indications.

Directions:

Spritz 1 time under the tongue 3 x per day until improvement is seen, dose once each time symptoms return.

Keep out of reach of children.

WARNINGS

If no improvement is seen after 7 days or new symptoms develop, discontinue use.

Active ingredients:

listed for each remedy.

Inactive Ingredients:

In reverse osmosis water with less than 1% alcohol.